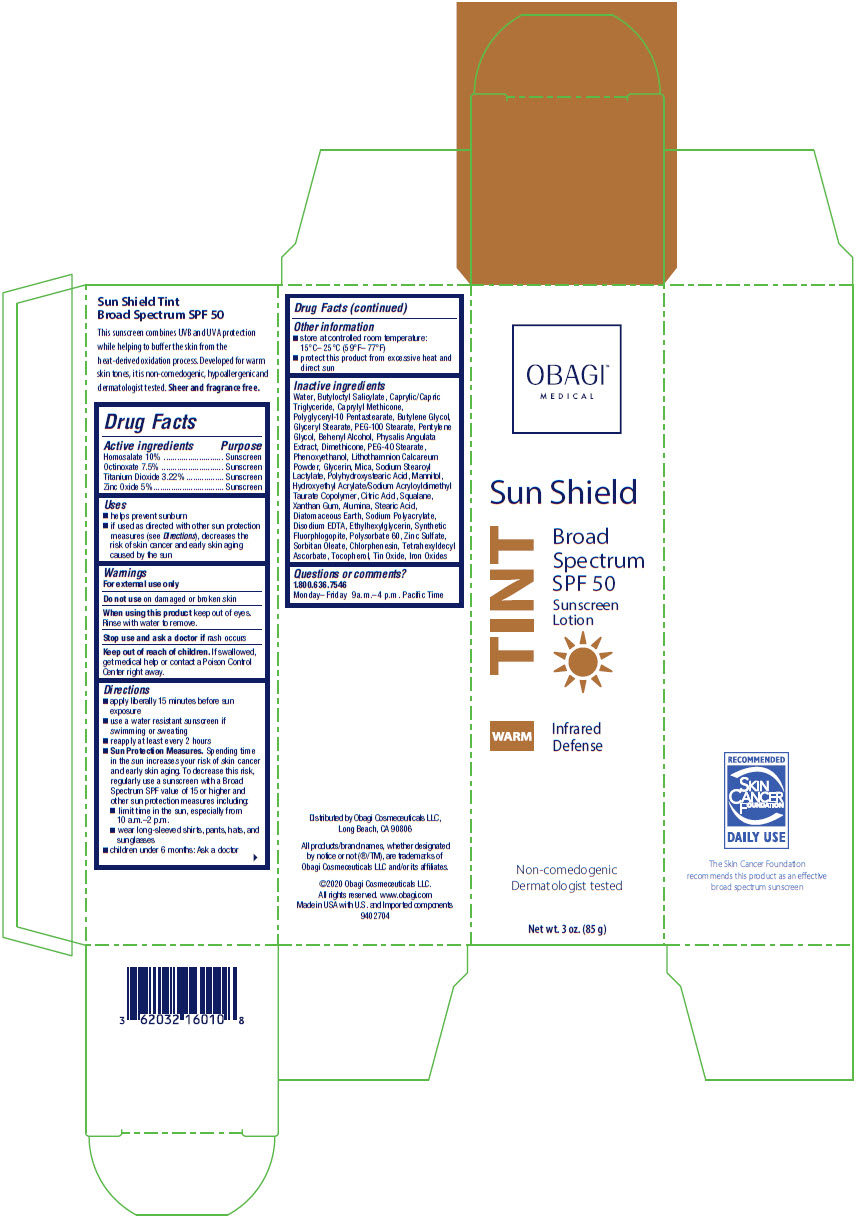 DRUG LABEL: Obagi
NDC: 62032-160 | Form: LOTION
Manufacturer: Obagi Cosmeceuticals LLC
Category: otc | Type: HUMAN OTC DRUG LABEL
Date: 20210211

ACTIVE INGREDIENTS: HOMOSALATE 8.5 g/85 g; OCTINOXATE 6.375 g/85 g; TITANIUM DIOXIDE 2.737 g/85 g; ZINC OXIDE 4.25 g/85 g
INACTIVE INGREDIENTS: WATER; BUTYLOCTYL SALICYLATE; MEDIUM-CHAIN TRIGLYCERIDES; CAPRYLYL TRISILOXANE; 12-OXOOCTADECANOIC ACID; GLYCERYL MONOSTEARATE; PEG-100 STEARATE; BUTYLENE GLYCOL; PENTYLENE GLYCOL; DOCOSANOL; FERRIC OXIDE RED; PEG-40 STEARATE; DIMETHICONE; PHYSALIS ANGULATA WHOLE; PHENOXYETHANOL; FUCUS VESICULOSUS; GLYCERIN; MICA; SODIUM STEAROYL LACTYLATE; POLYHYDROXYSTEARIC ACID (2300 MW); MANNITOL; HYDROXYETHYL ACRYLATE/SODIUM ACRYLOYLDIMETHYL TAURATE COPOLYMER (100000 MPA.S AT 1.5%); ANHYDROUS CITRIC ACID; SQUALANE; ALUMINUM OXIDE; STEARIC ACID; XANTHAN GUM; DIATOMACEOUS EARTH; SODIUM POLYACRYLATE (2500000 MW); EDETATE DISODIUM; ETHYLHEXYLGLYCERIN; POLYSORBATE 60; ZINC SULFATE, UNSPECIFIED FORM; CHLORPHENESIN; TETRAHEXYLDECYL ASCORBATE; STANNIC OXIDE; TOCOPHEROL; EDETATE DISODIUM ANHYDROUS; FERROUS OXIDE; PHYMATOLITHON CALCAREUM; POLYGLYCERYL-10 PENTASTEARATE; SORBITAN MONOOLEATE; MAGNESIUM POTASSIUM ALUMINOSILICATE FLUORIDE; ZINC SULFATE MONOHYDRATE

OBAGI®
Sun Shield TINT Warm Sunscreen
Broad Spectrum SPF 50

Drug Facts

ACTIVE INGREDIENT

Active ingredients | Purpose
Homosalate 10%; Octinoxate 7.5%; Titanium dioxide 3.22% | Sunscreen; Sunscreen; Sunscreen
Zinc oxide 5% | Sunscreen

Uses

- helps prevent sunburn
- if used as directed with other sun protection measures (see Directions), decreases the risk of skin cancer and early skin aging caused by the sun

Warnings

- For external use only
- Do not use on damaged or broken skin
- When using this product keep out of eyes. Rinse with water to remove.
- Stop use and ask a doctor if rash occurs
- Keep out of reach of children. If swallowed, get medical help or contact a Poison Control Center right away.

Directions

- apply liberally 15 minutes before sun exposure
- use a water resistant sunscreen if swimming or sweating
- reapply at least every 2 hours
- Sun Protection Measures. Spending time in the sun increases your risk of skin cancer and early skin aging. To decrease this risk, regularly use a sunscreen with a Broad Spectrum SPF value of 15 or higher and other sun protection measures including:
  - limit time in the sun, especially from 10 a.m.-2 p.m.
  - wear long-sleeved shirts, pants, hats and sunglasses
- children under 6 months: ask a doctor

Other information

- store at controlled room temperature: 15°C–25°C (59°F–77°F)
- protect this product from excessive heat and direct sun

Inactive ingredients

Water, Butyloctyl Salicylate, Caprylic/Capric Triglyceride, Caprylyl Methicone, Polyglyceryl-10 Pentastearate, Butylene Glycol, Glyceryl Stearate, PEG-100 Stearate, Pentylene Glycol, Behenyl Alcohol, Physalis Angulata Extract, Dimethicone, PEG-40 Stearate, Phenoxyethanol, Lithothamnion Calcareum Powder, Glycerin, Mica, Sodium Stearoyl Lactylate, Polyhydroxystearic Acid, Mannitol, Hydroxyethyl Acrylate/Sodium Acryloyldimethyl Taurate Copolymer, Citric Acid, Squalane, Xanthan Gum, Alumina, Stearic Acid, Diatomaceous Earth, Sodium Polyacrylate, Disodium EDTA, Ethylhexylglycerin, Synthetic Fluorphlogopite, Polysorbate 60, Zinc Sulfate, Sorbitan Oleate, Chlorphenesin, Tetrahexyldecyl Ascorbate, Tocopherol, Tin Oxide, Iron Oxides

Questions or comments?

1.800.636.7546

Monday–Friday 9 a.m.–4 p.m. Pacific Time

Distributed by Obagi Cosmeceuticals LLC,
Long Beach, CA 90806

PRINCIPAL DISPLAY PANEL - 85 g Tube Carton

OBAGI™
MEDICAL

Sun Shield

Broad
Spectrum
SPF 50
Sunscreen
Lotion

WARM
TINT

Infrared
Defense

Non-comedogenic
Dermatologist tested

Net wt. 3 oz. (85 g)